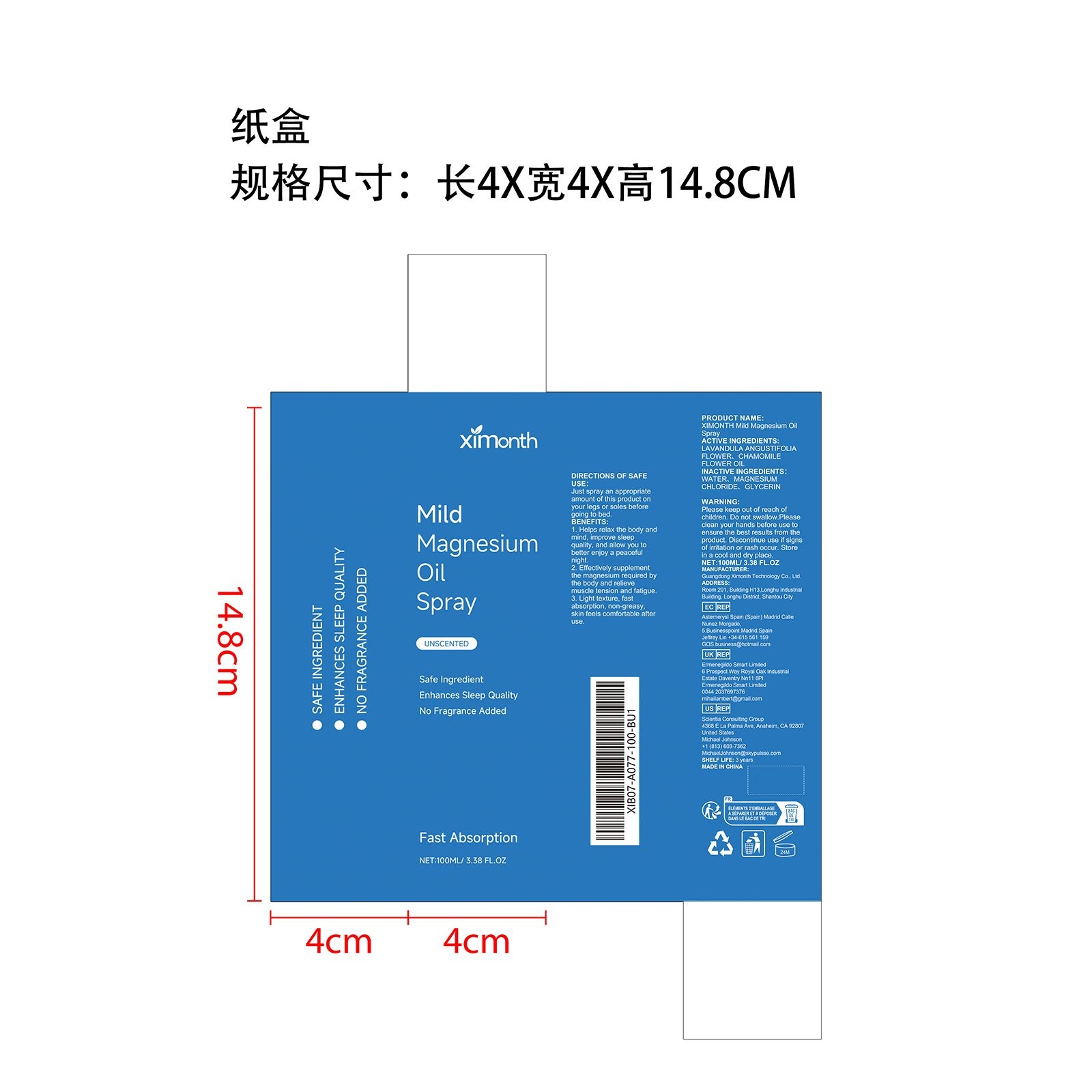 DRUG LABEL: XIMONTH Mild Magnesium Oil
NDC: 84660-046 | Form: SPRAY
Manufacturer: Guangdong Ximonth Technology Co., Ltd.
Category: otc | Type: HUMAN OTC DRUG LABEL
Date: 20241018

ACTIVE INGREDIENTS: CHAMOMILE FLOWER OIL 15 mg/100 mg; LAVANDULA ANGUSTIFOLIA FLOWER 30 mg/100 mg
INACTIVE INGREDIENTS: WATER 30 mg/100 mg; GLYCERIN 15 mg/100 mg; MAGNESIUM CHLORIDE 10 mg/100 mg

ACTIVE INGREDIENTS

LAVANDULA ANGUSTIFOLIA WHOLE、CHAMOMILE

PURPOSE

1. Rich in pure plant ingredients, it helps moisturize dry skin and gives you brighter skin.
2. The texture of this product is
refreshing and non-greasy, with no sticky residue or heavy feeling, keeping your skin moisturized and smooth all
day long.
3. In autumn and winter, this product will keep your skin away from dryness and help you spend this autumn and
winter refreshingly.
4. Suitable for all types of skin, makes skin look translucent and makes you look younger.

USE

1. Clean and dry body
2. Take an appropriate amount of this product and apply it evenly on the skin
3. Massage gently in circular motions for absorption.

WARNINGS

Please keep out of reach of children. Do not swallow.Please clean your hands before use to ensure the best results from the product. Discontinue use if signs of irritation or rash occur. Store in a cool and dry place.

DO NOT USE

Discontinue use if signs of irritation or rash occur.

STOP USE

Discontinue use if signs of irritation or rash occur.

KEEP OUT OF REACH OF CHILDREN

Please keep out of reach of children. Do not swallow.

STORAGE AND HANDLING

Store in a cool and dry place.

INACTIVE INGREDIENT

WATER、MAGNESIUM CHLORIDE、GLYCERIN